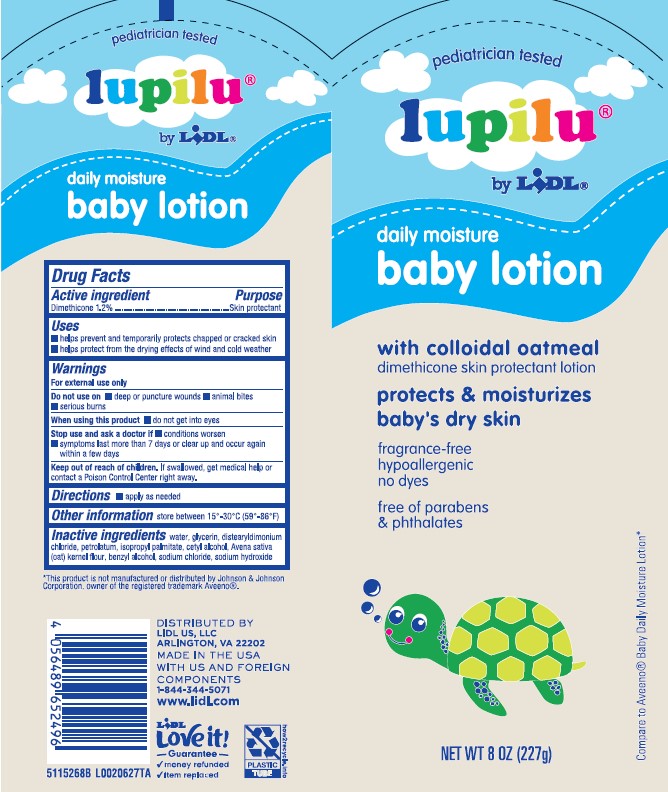 DRUG LABEL: Daily Moisturizing
NDC: 71141-496 | Form: LOTION
Manufacturer: Lidl US, LLC
Category: otc | Type: HUMAN OTC DRUG LABEL
Date: 20260204

ACTIVE INGREDIENTS: DIMETHICONE 12 mg/1 g
INACTIVE INGREDIENTS: WATER; GLYCERIN; DISTEARYLDIMONIUM CHLORIDE; PETROLATUM; ISOPROPYL PALMITATE; CETYL ALCOHOL; OATMEAL; BENZYL ALCOHOL; SODIUM HYDRIDE

Lupilu 496.001/496AA
Daily Baby Lotion with Colloidal Oatmeal

Claims

pediatrician tested

lupilu®by LIDL

Active Ingredient

Dimethicone 1.2%

Purpose

Skin Protectant

Uses

- helps prevent and temporarily protects chafed, chapped or cracked skin
- helps protect from the drying effects of wind and cold weather

Warnings

For external use only

Do not use on

- deep or puncture wounds
- animal bites
- serious burns

When using this product

- do not get into eyes

Stop Use and ask a doctor is

- condition worsens
- symptoms last more than 7 days or clear up and occur again within a few days

Keep out of reach of children.

If swallowed, get medical help or contact a Poison Control Center right away.

Directions

- apply as needed

Other Information

store between 15°-30°C (59°-86°F)

Inactive ingredients

water, glycerin, distearyldimonium chloride, petrolatum, isopropyl palmitate, cetyl alcohol, Avena sativa (oat) kernel flour, benzyl alcohol, sodium chloride, sodium hydroxide

Disclaimer

*This product is not manufactured or distributed by Johnson & Johnson Corporation, owner of the registered trademark Aveeno.

ADVERSE REACTIONS SECTION

DISTRIBUTED BY

LIDL US, LLC

Arlington, VA 22202

MADE IN THE USA WITH US AND FOREIGN COMPONENTS

1-844-344-5071

www.lidl.com

LIDL Love it! Guarantee

- money refunded
- item replaced

PLASTIC TUBE

howtorecycle.info

principal display panel

pediatrician tested

lupilu®

by LIDL®

daily moisture

baby lotion

with colloidal oatmeal

dimethicone skin protectant lotion

protects & moisturizes babys dry skin

Fragrance-free

hypoallergenic

no dyes

free of parabens & phthalates

Compare to Aveeno®Baby Daily Moisture Lotion*

NET WT 8 OZ (227g)